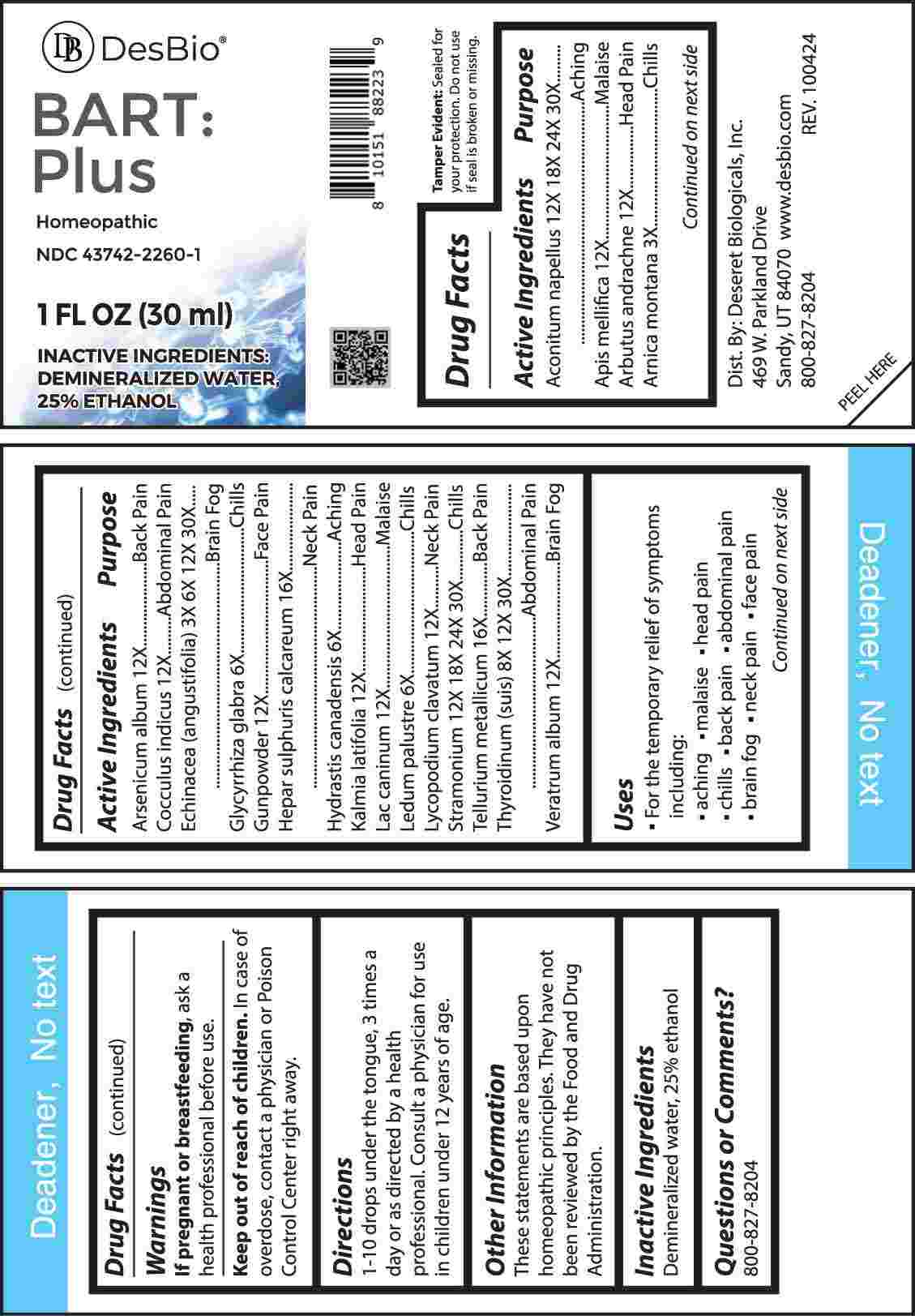 DRUG LABEL: BART PLUS
NDC: 43742-2260 | Form: LIQUID
Manufacturer: Deseret Biologicals, Inc.
Category: homeopathic | Type: HUMAN OTC DRUG LABEL
Date: 20250304

ACTIVE INGREDIENTS: ACONITUM NAPELLUS WHOLE 12 [hp_X]/1 mL; APIS MELLIFERA 12 [hp_X]/1 mL; ARBUTUS ANDRACHNE LEAFY SHOOT 12 [hp_X]/1 mL; ARNICA MONTANA WHOLE 3 [hp_X]/1 mL; ARSENIC TRIOXIDE 12 [hp_X]/1 mL; ANAMIRTA COCCULUS SEED 12 [hp_X]/1 mL; ECHINACEA ANGUSTIFOLIA WHOLE 3 [hp_X]/1 mL; GLYCYRRHIZA GLABRA 6 [hp_X]/1 mL; POTASSIUM NITRATE 12 [hp_X]/1 mL; CALCIUM SULFIDE 16 [hp_X]/1 mL; GOLDENSEAL 6 [hp_X]/1 mL; KALMIA LATIFOLIA LEAF 12 [hp_X]/1 mL; CANIS LUPUS FAMILIARIS MILK 12 [hp_X]/1 mL; RHODODENDRON TOMENTOSUM LEAFY TWIG 6 [hp_X]/1 mL; LYCOPODIUM CLAVATUM SPORE 12 [hp_X]/1 mL; DATURA STRAMONIUM 12 [hp_X]/1 mL; TELLURIUM 16 [hp_X]/1 mL; THYROID 8 [hp_X]/1 mL; VERATRUM ALBUM ROOT 12 [hp_X]/1 mL
INACTIVE INGREDIENTS: WATER; ALCOHOL

DRUG FACTS:

ACTIVE INGREDIENTS:

Aconitum Napellus12X, 18X, 24X, 30X, Apis Mellifica 12X, Arbutus Andrachne 12X, Arnica Montana 3X, Arsenicum Album 12X, Cocculus Indicus 12X, Echinacea (Angustifolia) 3X, 6X, 12X, 30X, Glycyrrhiza Glabra 6X, , Gunpowder 12X, Hepar Sulphuris Calcareum 16X, Hydrastis Canadensis 6X, Kalmia Latifolia 12X, Lac Caninum 12X, Ledum Palustre 6X, Lycopodium Clavatum 12X, Stramonium 12X, 18X, 24X, 30X, Tellurium Metallicum 16X, Thyroidinum (Suis) 8X, 12X, 30X, Veratrum Album 12X.

PURPOSE:

Aconitum Napellus - Aching, Apis Mellifica - Malaise, Arbutus Andrachne – Head Pain, Arnica Montana - Chills, Arsenicum Album – Back Pain, Cocculus Indicus – Abdominal Pain, Echinacea (Angustifolia) – Brain Fog, Glycyrrhiza Glabra - Chills, Gunpowder – Face Pain, Hepar Sulphuris Calcareum – Neck Pain, Hydrastis Canadensis - Aching, Kalmia Latifolia – Head Pain, Lac Caninum - Malaise, Ledum Palustre - Chills, Lycopodium Clavatum – Neck Pain, Stramonium - Chills, Tellurium Metallicum – Back Pain, Thyroidinum (Suis) – Abdominal Pain, Veratrum Album – Brain Fog

USES:

• For the temporary relief of symptoms including:

• aching • malaise • head pain • chills • back pain

• abdominal pain • brain fog • neck pain • face pain

These statements are based upon homeopathic principles. They have not been reviewed by the Food and Drug Administration.

WARNINGS:

If pregnant or breastfeeding, ask a health professional before use.

Keep out of reach of children. In case of overdose, contact a physician or Poison Control Center right away.
Tamper Evident: Sealed for your protection. Do not use if seal is broken or missing.

KEEP OUT OF REACH OF CHILDREN:

In case of overdose, contact a physician or Poison Control Center right away.

DIRECTIONS:

1-10 drops under the tongue, 3 times a day or as directed by a health professional. Consult a physician for use in children under 12 years of age.

INACTIVE INGREDIENTS:

Demineralized water, 25% ethanol

QUESTIONS:

Dist. By: Deseret Biologicals, Inc.
469 W. Parkland Drive
Sandy, UT 84070

www.desbio.com

800-827-8204

PACKAGE LABEL DISPLAY:

DesBio

BART:Plus

Homeopathic

NDC 43742-2260-1

1 FL OZ (30 ml)